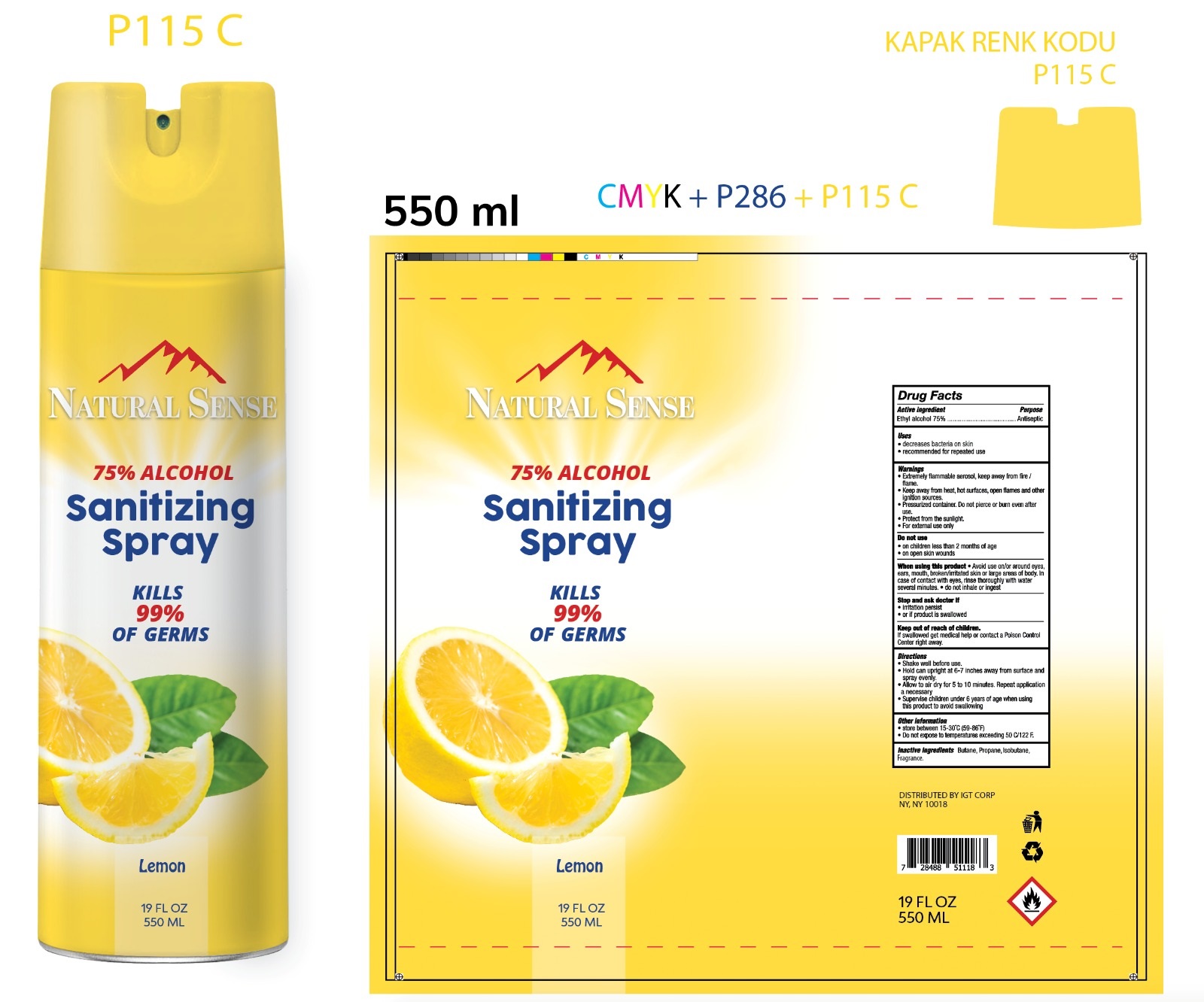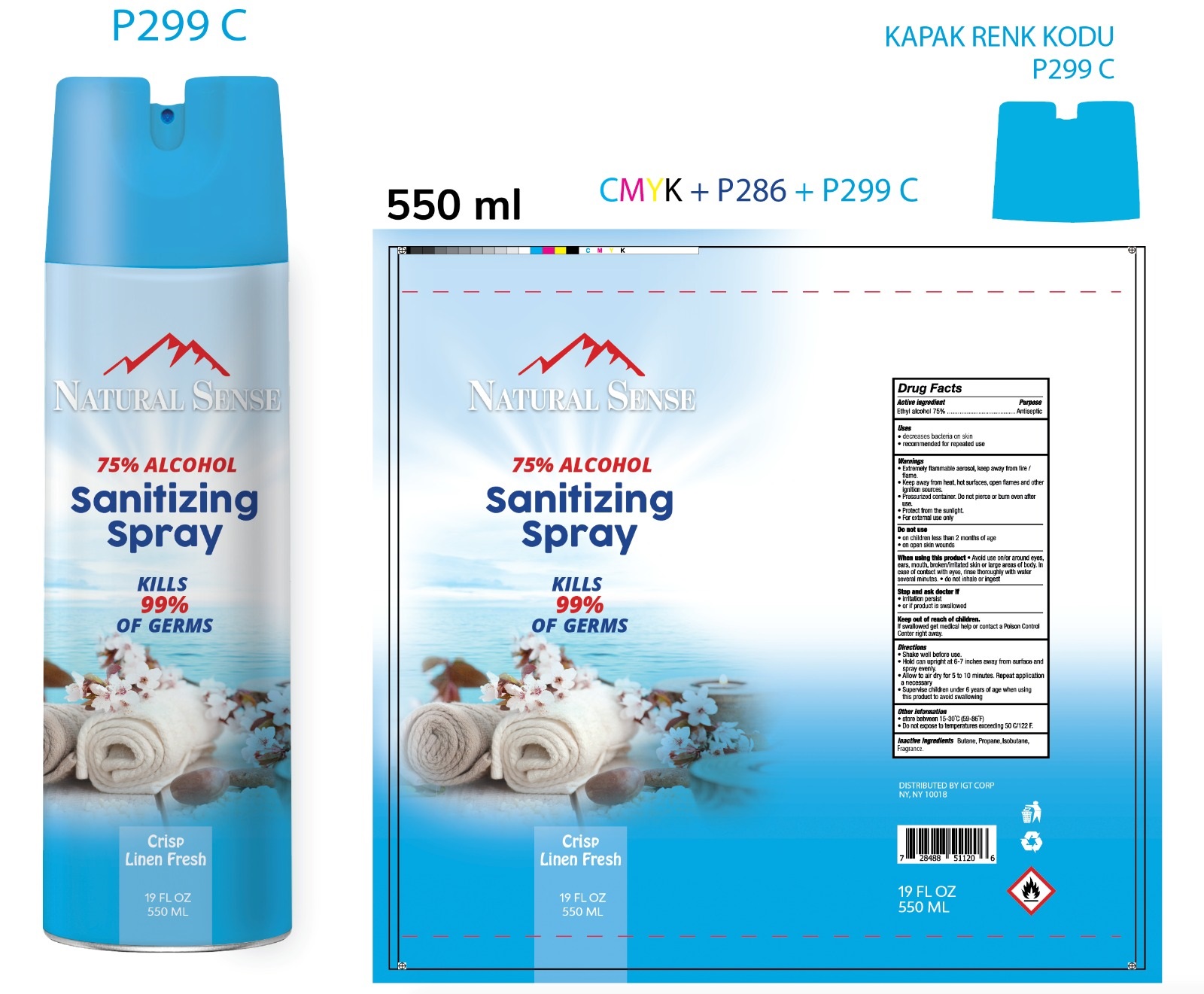 DRUG LABEL: NATURAL SENSE
NDC: 78440-002 | Form: AEROSOL, SPRAY
Manufacturer: INTERNATIONAL GENERAL TRADING CORP
Category: otc | Type: HUMAN OTC DRUG LABEL
Date: 20200921

ACTIVE INGREDIENTS: ALCOHOL 75 mL/100 mL
INACTIVE INGREDIENTS: PROPANE 6.22 mL/100 mL; ISOBUTANE 4.345 mL/100 mL; BUTANE 14 mL/100 mL

NATURAL SENSE SPRAY

This is a hand sanitizer manufactured according to the Temporary Policy for Preparation of Certain Alcohol-Based Hand Sanitizer Products During the Public Health Emergency (CoViD-19); Guidance for Industry.

The hand sanitizer is manufactured using only the following United States Pharmacopoeia (USP) grade ingredients in the preparation of the product (percentage in final product formulation) consistent with World Health Organization (WHO) recommendations:

1. Alcohol (ethanol) (USP or Food Chemical Codex (FCC) grade) (80%, volume/volume (v/v)) in an aqueous solution denatured according to Alcohol and Tobacco Tax and Trade Bureau regulations in 27 CFR part 20.
2. Glycerol (1.45% v/v).
3. Hydrogen peroxide (0.125% v/v).
4. Sterile distilled water or boiled cold water.

The firm does not add other active or inactive ingredients. Different or additional ingredients may impact the quality and potency of the product.

Active Ingredient(s)

ETHYL ALCOHOL 75%

Purpose

Antiseptic, Hand Sanitizer

Use

Decreases bacteria on skin

Recommended for repeat use

Warnings

-Extremely flammable aerosol, keep away from fire and flame

-Keep away from heat, hot surfaces, open flames and other ignition sources

-Pressurized container. Do not pierce or burn even after use

-Protect from sunlight

-For external use only

Do not use

- in children less than 2 months of age
- on open skin wounds

When using this product keep out of eyes, ears, and mouth. In case of contact with eyes, rinse eyes thoroughly with water.
Stop use and ask a doctor if irritation or rash occurs. These may be signs of a serious condition.
Keep out of reach of children. If swallowed, get medical help or contact a Poison Control Center right away.

STOP USE

-IRRITATION PERSIST

OR IF PRODUCT IS SWALLOWED

Keep out of reach of children. If swallowed, get medical help or contact a Poison Control Center right away.

Directions

-SHAKE WELL BEFORE USE

HOLD CAN UPRIGHT AT 6-7 INCHES AWAY FROM SURFACE AND SPRAY EVENLY

ALLOW TO AIR DRY FOR 5-10 MINUTS REPEAT IF NECCESARRY

SUPERVISE CHILDREN UNDER 6 YEARS

Other information

- Store between 15-30C (59-86F)
- Avoid freezing and excessive heat above 40C (104F)

Inactive ingredients

BUTANE, PROPANE, ISO BUTANE, FRAGANCE

Package Label - Principal Display Panel

550 ML 78440-001-01